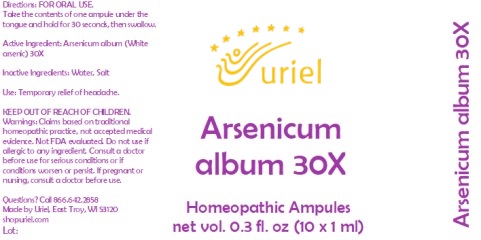 DRUG LABEL: Arsenicum album 30X
NDC: 48951-1365 | Form: LIQUID
Manufacturer: Uriel Pharmacy, Inc.
Category: homeopathic | Type: HUMAN OTC DRUG LABEL
Date: 20231005

ACTIVE INGREDIENTS: ARSENIC TRIOXIDE 30 [hp_X]/1 mL
INACTIVE INGREDIENTS: SODIUM CHLORIDE; WATER

Arsenicum album 30X

INDICATIONS AND USAGE

Directions: FOR ORAL USE.

DOSAGE AND ADMINISTRATION

Take the contents of one ampule under the tongue and hold for 30 seconds, then swallow.

Active Ingredient: Arsenicum album (White arsenic) 30X

PURPOSE

Use: Temporary relief of headache.

KEEP OUT OF REACH OF CHILDREN.

WARNINGS

Warnings: Claims based on traditional homeopathic practice, not accepted medical evidence. Not FDA evaluated. Do not use if allergic to any ingredient. Consult a doctor before use for serious conditions or if conditions worsen or persist. If pregnant or nursing, consult a doctor before use.

Questions? Call 866.642.2858
Made by Uriel, East Troy, WI 53120
shopuriel.com Lot:

Inactive Ingredients: Water, Salt